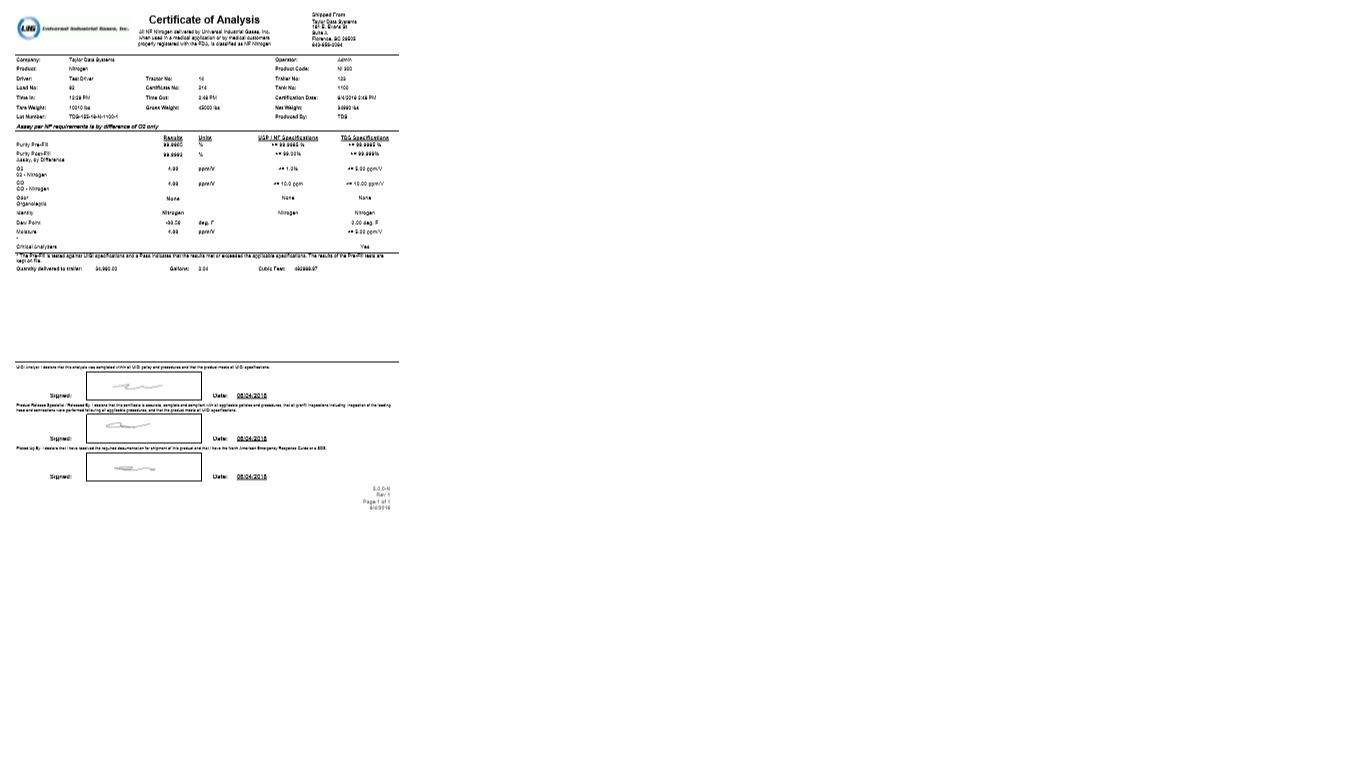 DRUG LABEL: Nitrogen
NDC: 72457-005 | Form: GAS
Manufacturer: UCG Georgia, LLC
Category: prescription | Type: HUMAN PRESCRIPTION DRUG LABEL
Date: 20251210

ACTIVE INGREDIENTS: NITROGEN 995 mL/1 L

Nitrogen

PACKAGE LABEL

UIG Universal Industrial Gases, Inc

Certificate of Analysis

All NF Nitrogen delivered by Universal Industrial Gases, Inc, when used in a medical application or by medical customers properly registered with the FDA, is classified as NF Nitrogen

Shipped From

Taylor Data Systems

181 E. Evans St

Suite A

Florence, SC 29505

843-656-2084

Company: Taylor Data Systems Operator: Admin

Product: Nitrogen Product Code: NI 300

Driver: Test Driver Tractor No: 14 Trailer No: 123

Load No: 92 Certificate No: 214 Tank No: 1100

Time In: 12:29 PM Time Out: 2:48 PM Certification Date: 6/4/2018 2:48 PM

Tare Weight: 10010 lbs Gross Weight: 45000 lbs Net Weight: 34990 lbs

Lot Number: TDS-155-18-N-1100-1 Produced By: TDS

Assay per NF requirements is by difference of O2 only

Results Units USP/NF Specifications TDS Specifications

Purity Pre-fill 99.9985 % >=99.9985 % >=99.9985 %

Purity Post fill 99.9992 % >=99.00 % >=99.999 %

Assay, by Difference

O2 4.00 ppm/V <=1.0 % <=5.00 ppm/V

O2-Nitrogen

CO 4.00 ppm/V <=10.0 % <=10.00 ppm/V

CO-Nitrogen

Odor None None None

Organoleptic

Identity Nitrogen Nitrogen Nitrogen

Dew Point -88.50 deg. F 0.00 deg. F

Moisture 4.00 ppm/V <=5.00 ppm/V

-

Critical Analyzers Yes

*The Pre-Fill is tested against UIGI specifications and a Pass indicates that the results met or exceeded the applicable specifications. The results of the Pre-Fill tests are kept on file.

Quantity delivered to trailer: 34,990.00 Gallons: 2.04 Cubic Feet: 482966.97

UIGI Analyst: I declare that this analysis was completed within all UIGI policy and procedures and that the product meets all UIGI specifications.

Signed: Date: 06/04/2018

Product Release Specialist / Released By: I declare that this certificate is accurate, complete and compliant with all applicable policies and procedures, that all pre-fill inspections including inspection of the loading hose and connections were performed following all applicable procedures, and that the product meets all UIGI specifications.

Signed: Date: 06/04/2018

Picked Up By: I declare that I have received the required documentation for shipment of this product and that I have the North American Emergency Response Guide or a SDS.

Signed: Date: 06/04/2018